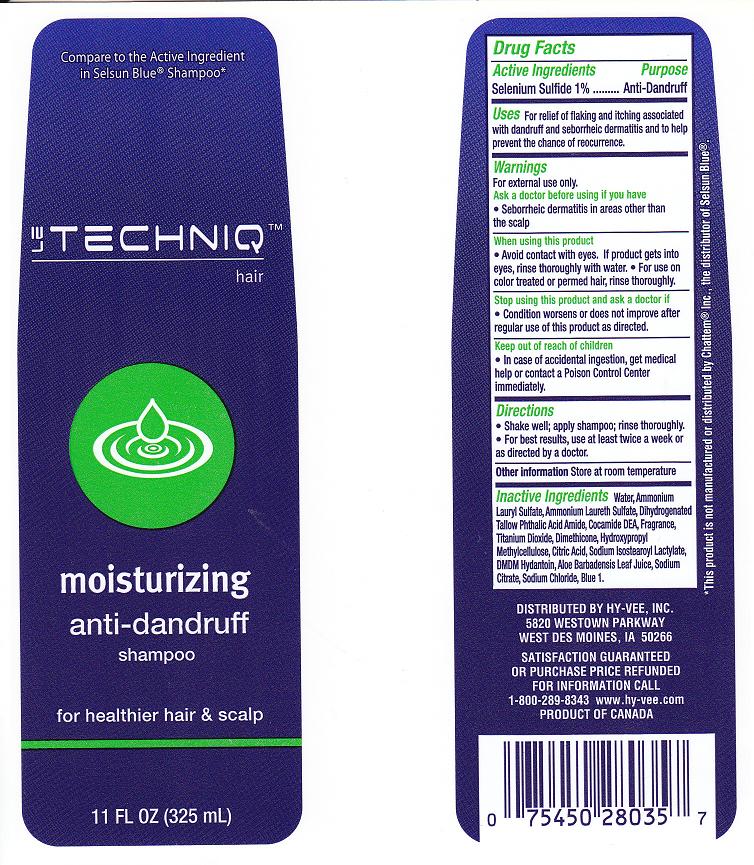 DRUG LABEL:  LeThechniq Dandruff
NDC: 42507-611 | Form: SHAMPOO
Manufacturer: HY-VEE, Inc
Category: otc | Type: HUMAN OTC DRUG LABEL
Date: 20101015

ACTIVE INGREDIENTS: SELENIUM SULFIDE 1 mL/100 mL
INACTIVE INGREDIENTS: WATER; AMMONIUM LAURYL SULFATE; AMMONIUM LAURETH-2 SULFATE; COCO DIETHANOLAMIDE; TITANIUM DIOXIDE; DIMETHICONE; HYPROMELLOSE 2208 (100 MPA.S); CITRIC ACID MONOHYDRATE; SODIUM ISOSTEAROYL LACTYLATE; DMDM HYDANTOIN; ALOE VERA LEAF; SODIUM CITRATE; SODIUM CHLORIDE; FD&C BLUE NO. 1

Active Ingredient

Selenium Sulfide 1%

Purpose

Anti-Dandruff

Uses

For relief of flaking, and itching associated with dandruff and seborrheic dermatitis and to help prevent the chance of re-occurence

Warnings

For external use only

Ask a doctor before using if you have

Seborrheic dermatitis in areas other than the scalp

When using this product

avoid contact with eyes. If contact occurs, rinse with water. For use on color treated or permed hair, rinse thoroughly

Stop using this product and ask doctor if

condition worsens or does not improve after regular use of this product as directed

Keep out of reach of children

In case of accidental ingestion, get medical help or contact a Poison Control Center immediately

Directions

- Shake well, apply shampoo, rinse thoroughly
- For best results, use at least twice a week or as directed by a doctor

Other information

Store at room temperature

Inactive Ingredients

Water (Aqua), Ammonium Lauryl Sulfate, Ammonium Laureth Sulfate, Dihydrogenated Tallow Phthalic Acid Amide, Cocamide DEA, Fragrance (Parfum), Titanium Dioxide, Dimethicone, Hydroxypropyl Methylcellulose, Citric Acid, Sodium Isostearoyl Lactylate, DMDM Hydantoin, Aloe Barbadensis Leaf Juice, Sodium Citrate, Sodium Chloride, Blue 1 (CI 42090)

Package Front and Back Labels

ra11.jpg